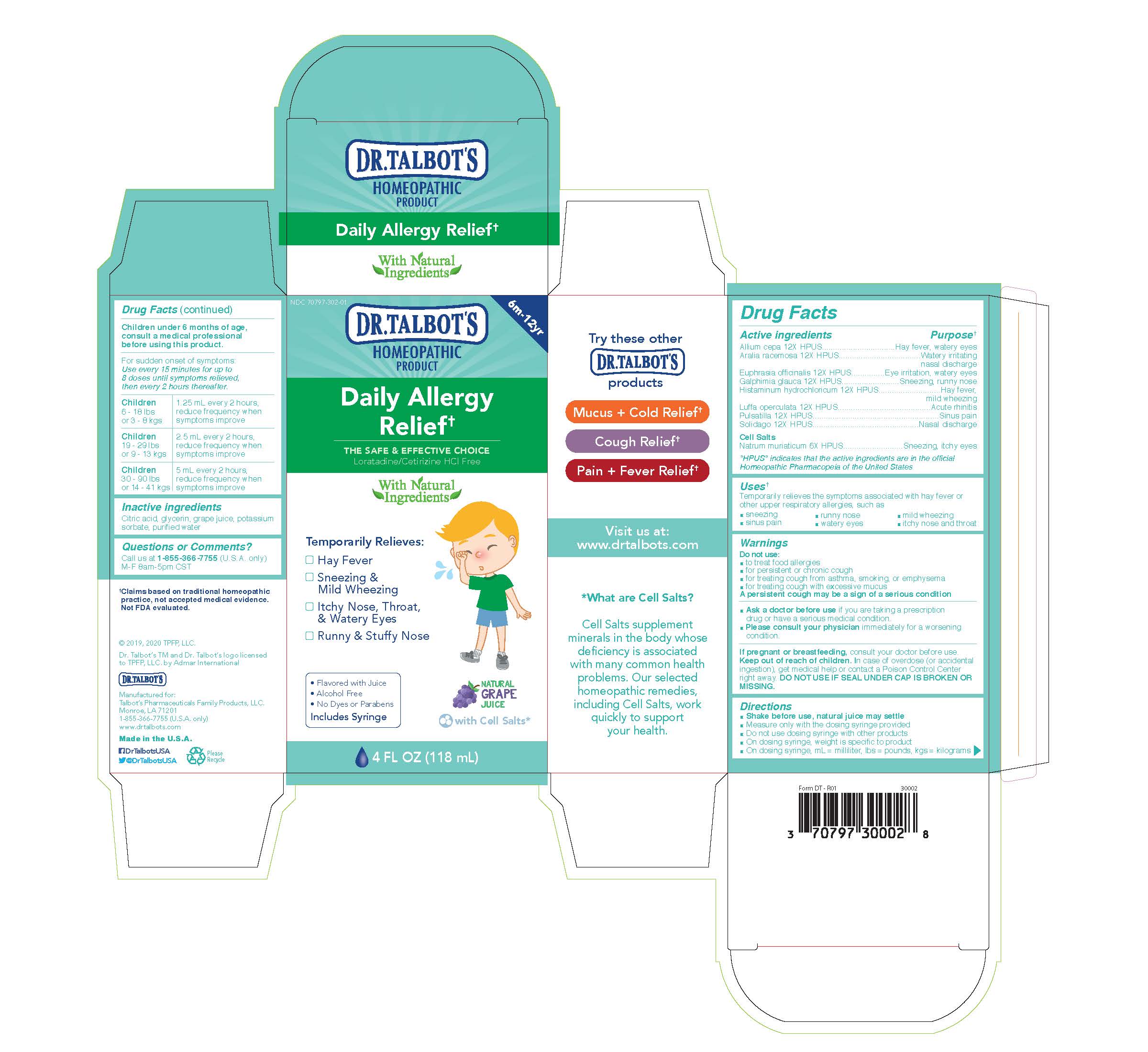 DRUG LABEL: Dr. Talbots Daily Allergy Relief
NDC: 70797-312 | Form: LIQUID
Manufacturer: Talbot's Pharmaceuticals Family Products, LLC.
Category: homeopathic | Type: HUMAN OTC DRUG LABEL
Date: 20211005

ACTIVE INGREDIENTS: ARALIA RACEMOSA ROOT 12 [hp_X]/118 mL; GALPHIMIA GLAUCA FLOWERING TOP 12 [hp_X]/118 mL; LUFFA OPERCULATA FRUIT 12 [hp_X]/118 mL; EUPHRASIA STRICTA 12 [hp_X]/118 mL; HISTAMINE DIHYDROCHLORIDE 12 [hp_X]/118 mL; ANEMONE PULSATILLA 12 [hp_X]/118 mL; ONION 12 [hp_X]/118 mL; SODIUM CHLORIDE 6 [hp_X]/118 mL; SOLIDAGO VIRGAUREA FLOWERING TOP 12 [hp_X]/118 mL
INACTIVE INGREDIENTS: POTASSIUM SORBATE; GLYCERIN; WATER; CITRIC ACID MONOHYDRATE; CONCORD GRAPE JUICE

Active Ingredients

Allium cepa 12X HPUS

Aralia racemosa 12X HPUS

Euphrasia officinalis 12X HPUS

Galphimia glauca 12X HPUS

Histaminum hydrochloricum 12X HPUS

Luffa operaculata 12X HPUS

Pulsatilla 12X HPUS

Solidago 12X HPUS

Cell Salts

Natrum muriaticum 6X HPUS

Purpose

Hay fever, watery eyes

Watery irritating nasal discharge

Eye irritation, watery eyes

Sneezing, runny nose

Hay fever, mild wheezing

Acute rhinitis

Sinus pain

Nasal discharge

Sneezing, itchy eyes

Pregnancy or breastfeeding

If pregnant or breastfeeding, consult your doctor before use.

Keep out of reach of children. in case of overdoes (or accidental ingestion), get medical help or contact a Poison Control Center right away. DO NOT USE IF SEAL UNDER CAP IS BROKEN OR MISSING.

Directions

- Shake before use, natural juice may settle
- Measure only with the dosing syringe provided
- Do not use dosing syringe with other products
- On dosing syringe, weight is specific to product
- On dosing syringe, ml = milliliter, lbs = pounds, kgs = kilograms

Children under 6 months of age, consult a medical professional before using this product.

For sudden onset of symptoms: Use every 15 minutes for up to 8 doses until symptoms relieved, then every 2 hours thereafter.

Children 6 - 18 lbs or 3 - 8 kgs

1.25 ml every 2 hours, reduce frequency when symptoms improve

Children 19 - 29 lbs or 9 - 13 kgs

2.5 ml every 2 hours, reduce frequency when symptoms improve

Children 30 - 90 lbs or 14 - 41 kgs

5 ml every 2 hours, reduce frequency when symptoms improve

Inactive Ingredients

Citric acid, glycerin, grape juice, potassium sorbate, purified water

Questions

Questions or Comments?

Call us at 1-800-588-6227

M-F 8am-5pm CST

Uses

Temporarily relieves the symptoms associated with hay fever or other upper respiratory allergies, such as

- sneezing
- sinus pain
- runny nose
- watery eyes
- mild wheezing
- itchy nose and throat

Warnings

Do not use:

- to treat food allergies
- for persistent or chronic cough
- for treating cough from asthma, smoking, or emphysema
- for treating cough with excessive mucus

A persistent cough may be a sign of a serious condition